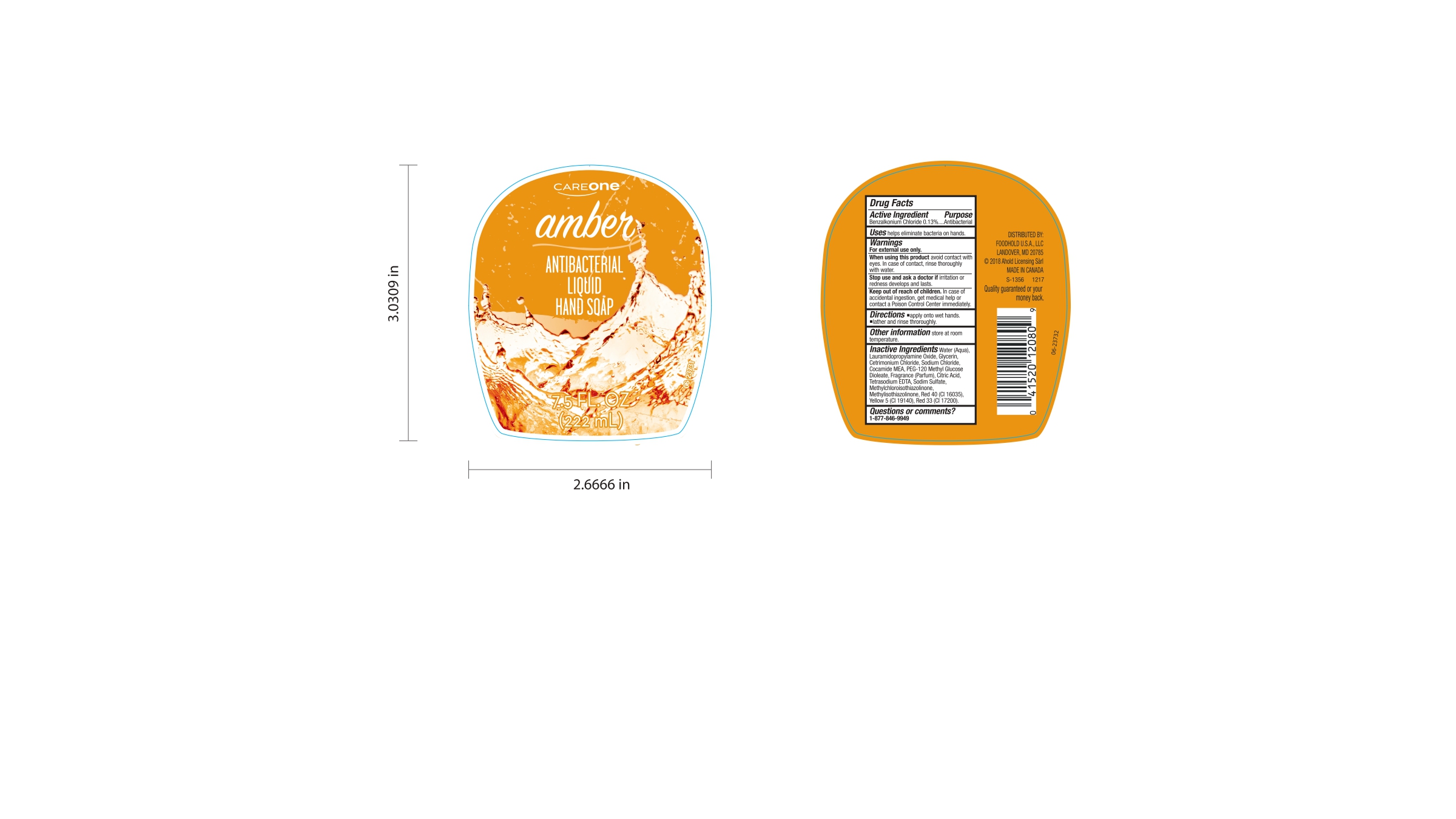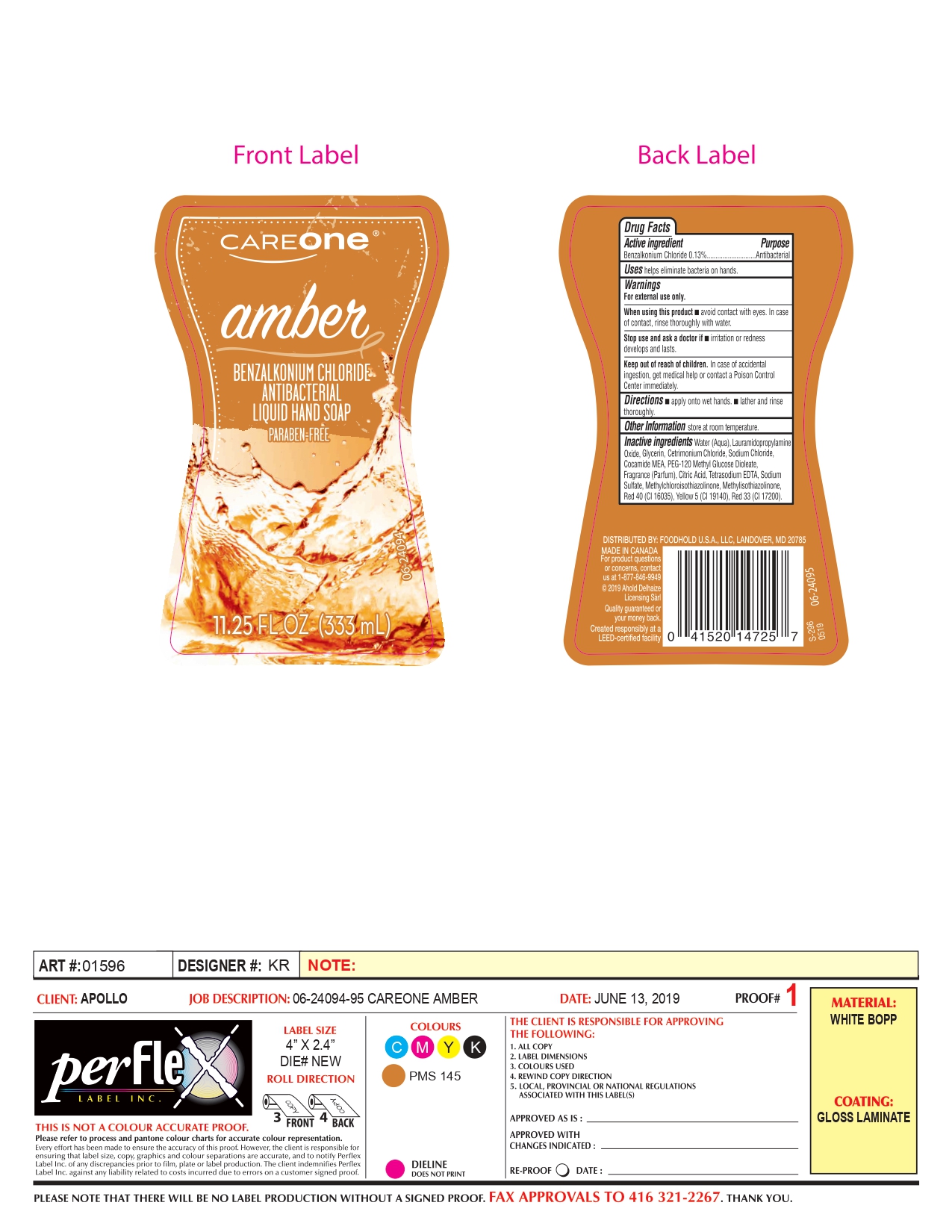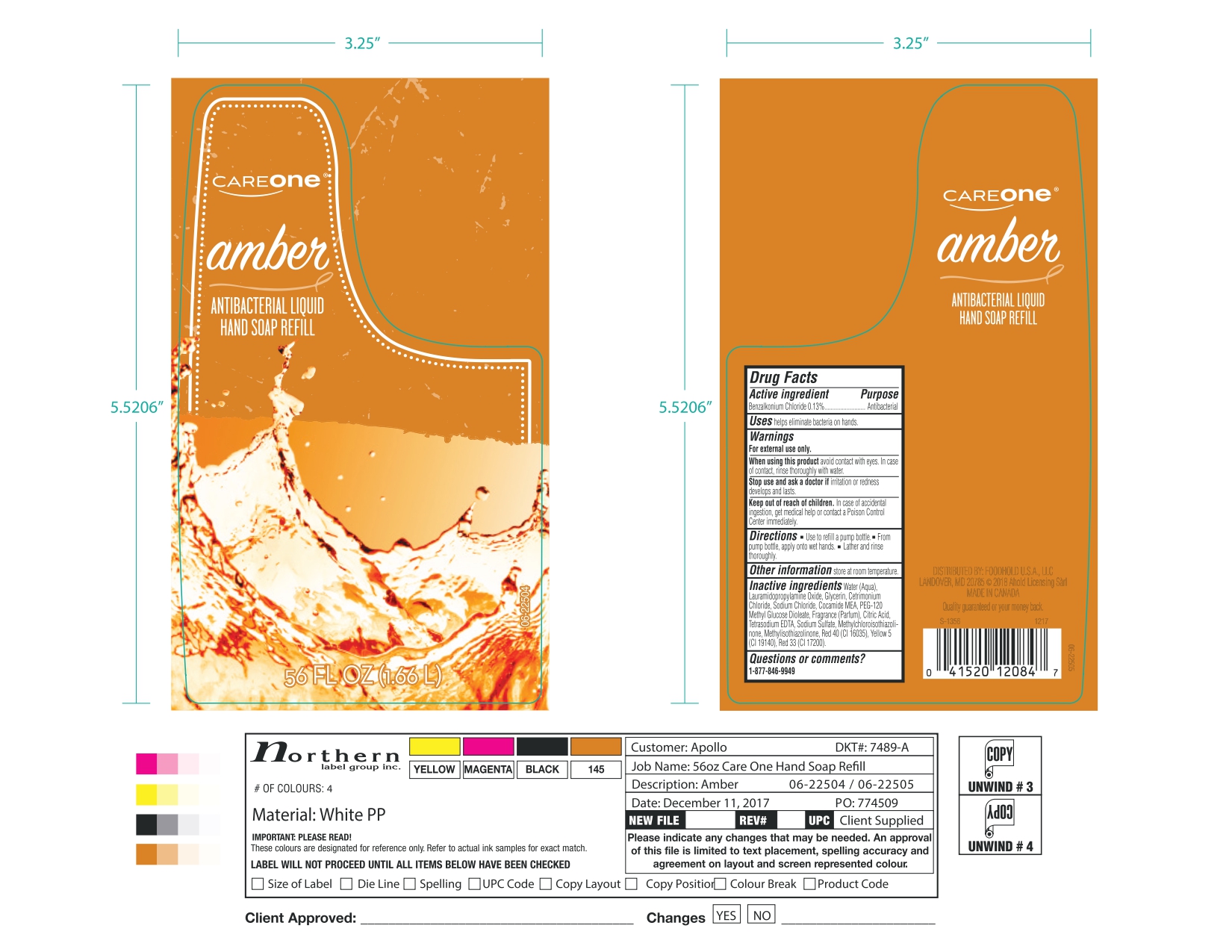 DRUG LABEL: Careone Amber
NDC: 72476-004 | Form: SOAP
Manufacturer: Retail Business Services, LLC
Category: otc | Type: HUMAN OTC DRUG LABEL
Date: 20241020

ACTIVE INGREDIENTS: BENZALKONIUM CHLORIDE 130 mg/100 mL
INACTIVE INGREDIENTS: COCO MONOETHANOLAMIDE; LAURAMIDOPROPYLAMINE OXIDE; SODIUM CHLORIDE; SODIUM SULFATE; METHYLCHLOROISOTHIAZOLINONE; METHYLISOTHIAZOLINONE; FD&C RED NO. 40; WATER; GLYCERIN; CETRIMONIUM CHLORIDE; PEG-120 METHYL GLUCOSE DIOLEATE; FRAGRANCE CLEAN ORC0600327; CITRIC ACID MONOHYDRATE; EDETATE SODIUM; FD&C YELLOW NO. 5; D&C RED NO. 33

72476-004- Careone Amber

Active Ingredient.

Benzalkonium Chloride (0.13%)

Purpose

Antibacterial

Uses

Helps eliminate bacteria on hands.

Warnings

For external use only

When using this product

Avoid contact with eyes. In case of contact, rinse thoroughly with water.

Stop use and ask a doctor.

If irritation or redness develops and lasts

Keep out of reach of children.

In case of accidental ingestion, get medical help or contact Poison Control Center immediately.

Directions

- apply onto wet hands (only for 222 ml and 333 ml)
- Lather and rinse thoroughly.(For all packages)
- From a pump bottle, apply onto wet hands (only for 1.66 L bottle)
- Use to refill a pump bottle (only for 1.66 L bottle)

Other Information

Store at Room Temperature

Inactive Ingredients

Water (Aqua), Lauramidopropylamine Oxide, Glycerin, Cetrimonium Chloride, Sodium Chloride, Cocamide MEA, PEG-120 Methyl Glucose Dioleate, Fragrance (Parfum), Citric Acid, Tetrasodium EDTA, Sodium Sulfate, Methylchloroisothiazolinone, Methylisothiazolinone, Red 40 (Cl 16035), Yellow 5 (Cl 19140), Red 33 (Cl 17200).

Questions or comments?

1-877-846-9949